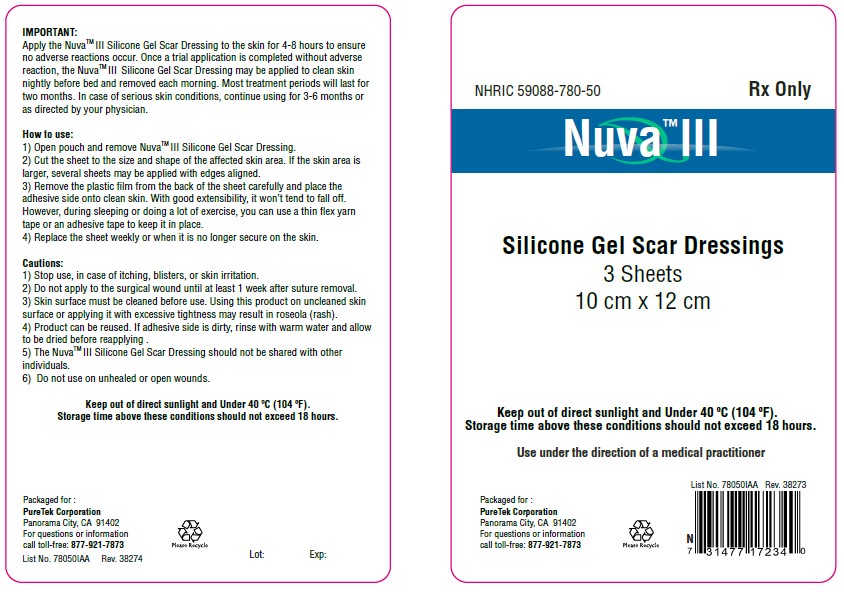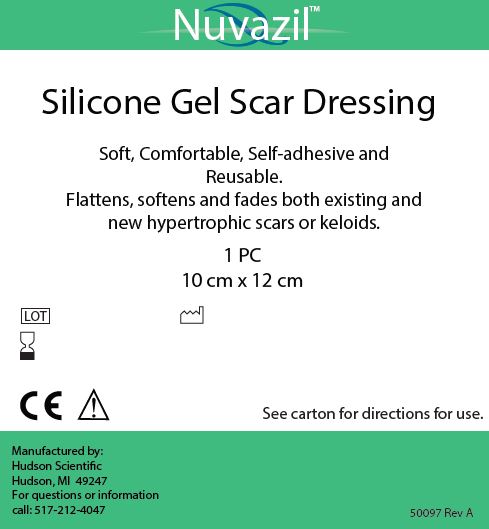 DRUG LABEL: Nuva III
NDC: 59088-780
Manufacturer: PureTek Corporation
Category: other | Type: MEDICAL DEVICE
Date: 20210318

Nuva™III

Rx Only

For external use only

Description

Nuva™III is a Silicone Gel Scar Dressing which is soft, comfortable, self-adhesive and Reusable.

Nuva™III flattens, softens and fades both existing and new hypertrophic scars or keloids.

Indications and Usage

For non-invasive management of both existing and new hypertrophic scars or keloids.

Use under the direction of a medical practitioner.

Contraindications:

Nuva™III is contraindicated for patients with sensitivity to silicone.

Warnings and Precautions:

For external use only.

1) Stop use, in case of itching, blisters, or skin irritation.
2) Do not apply to the surgical wound until at least 1 week after suture removal.
3) Skin surface must be cleaned before use. Using this product on uncleaned skin
surface or applying it with excessive tightness may result in roseola (rash).
4) Product can be reused. If adhesive side is dirty, rinse with warm water and allow
to be dried before reapplying .
5) The NuvaTMIII Silicone Gel Scar Dressing should not be shared with other
individuals.
6) Do not use on unhealed or open wounds.

Keep out of direct sunlight and Under 40°C (104 °F).

Storage time above these conditions should not exceed 18 hours.

Dosage & Administration:

Important:
Apply the Nuva™III Silicone Gel Scar Dressing to the skin for 4-8 hours to ensure no adverse reactions occur. Once a trial application is completed without adverse reaction, the Nuva™III Silicone Gel Scar Dressing may be applied to clean skin nightly before bed and removed each morning. Most treatment period will last for two months. In case of serious skin conditions, continue using for 3-6 months or as directed by your physician.

How to use:

1. Open pouch and remove Nuva™III Silicone Gel Scar Dressing.
2. Cut the sheet to the size and shape of the affected skin area. If the skin area is larger, several sheets may be applied with edges aligned.
3. Remove the plastic film from the back of the sheet carefully and place the adhesive side onto clean skin. With good extensibility, it won’t tend to fall off. However, during sleeping or doing a lot of exercise, you can use a thin flex yarn tape or an adhesive tape to keep it in place.
4. Replace the sheet weekly or when it is no longer secure on the skin.

How Supplied:

Nuva™III is provided in a shipping pouch containing three (3) individually wrapped pouches. Each pouch contains one Nuva™III 10 cm x 12 cm pad.

Storage and Handling:

Keep out of direct sunlight and under 40°C (104°F).

Storage time above these conditions should not exceed 18 hours.

Adverse Reactions:

In rare circumstances, use of Nuva™III may cause skin irritations including redness, stinging or other irritations. Those effects should go away after use of Nuva™III is discontinued.

Manufacturer:

Nuva™III is manufactured by:

Hudson Scientific LLC
103 W. Main St.
Hudson, MI 49247

Rx Only

Nuvazil™III Pouch Label

The label on each pouch containing a Nuvazil™III sheet is pictured below:

Nuva™III

Packaged for :
PureTek Corporation
Panorama City, CA 91402
For questions or information
call toll-free: 877-921-7873